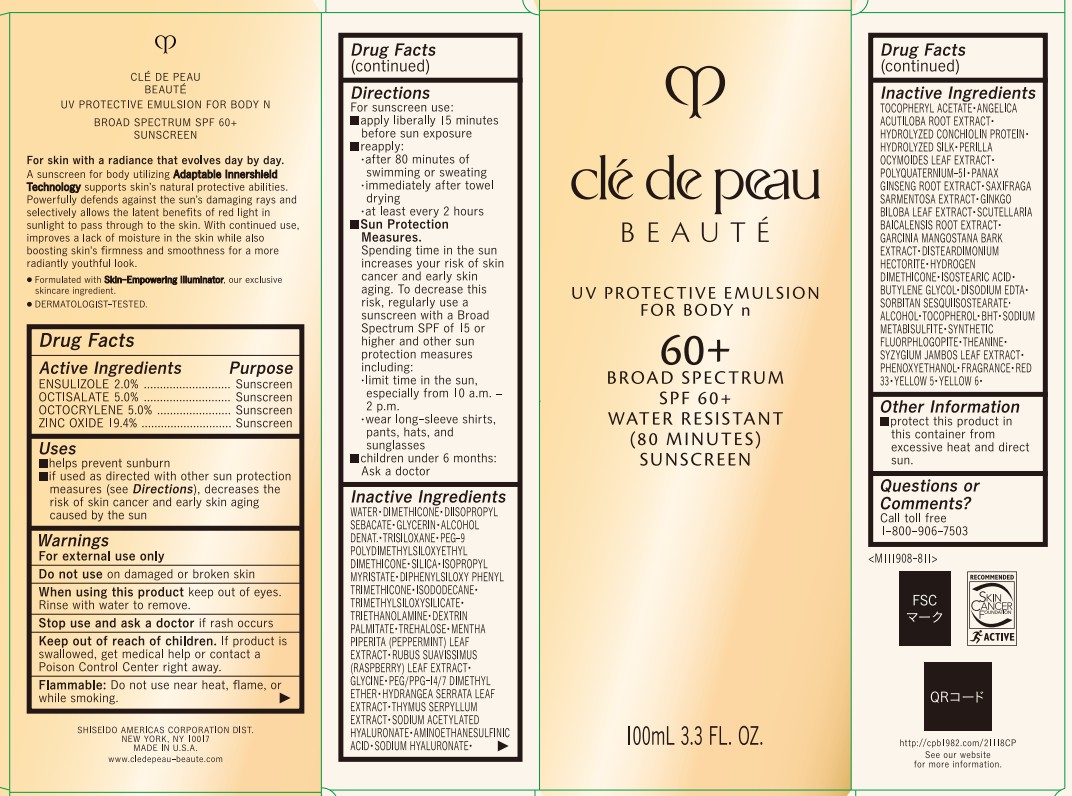 DRUG LABEL: cle de peau BEAUTE UV PROTECTIVE FOR BODY N
NDC: 58411-956 | Form: EMULSION
Manufacturer: Shiseido Americas Corporation
Category: otc | Type: HUMAN OTC DRUG LABEL
Date: 20251216

ACTIVE INGREDIENTS: ENSULIZOLE 2.384 g/100 mL; OCTISALATE 5.96 g/100 mL; OCTOCRYLENE 5.96 g/100 mL; ZINC OXIDE 23.1248 g/100 mL
INACTIVE INGREDIENTS: SCUTELLARIA BAICALENSIS ROOT; GARCINIA MANGOSTANA BARK; DISTEARDIMONIUM HECTORITE; HYDROGEN DIMETHICONE (13 CST); ISOSTEARIC ACID; BUTYLENE GLYCOL; EDETATE SODIUM; SORBITAN SESQUIISOSTEARATE; TOCOPHEROL; BUTYLATED HYDROXYTOLUENE; SODIUM METABISULFITE; MAGNESIUM POTASSIUM ALUMINOSILICATE FLUORIDE; THEANINE; SYZYGIUM JAMBOS LEAF; PHENOXYETHANOL; D&C RED NO. 33; FD&C YELLOW NO. 5; FD&C YELLOW NO. 6; WATER; DIMETHICONE; DIISOPROPYL SEBACATE; GLYCERIN; ALCOHOL; TRISILOXANE; PEG-9 POLYDIMETHYLSILOXYETHYL DIMETHICONE; SILICA; ISOPROPYL MYRISTATE; DIPHENYLSILOXY PHENYL TRIMETHICONE; ISODODECANE; TRIMETHYLSILOXYSILICATE (M/Q 0.6-0.8); TRIETHANOLAMINE; DEXTRIN PALMITATE (CORN; 20000 MW); TREHALOSE; MENTHA PIPERITA (PEPPERMINT) LEAF; RUBUS CHINGII VAR. SUAVISSIMUS LEAF; GLYCINE; PEG/PPG-14/7 DIMETHYL ETHER; HYDRANGEA SERRATA LEAF; THYMUS SERPYLLUM; SODIUM ACETYLATED HYALURONATE; AMINOETHANESULFINIC ACID; SODIUM HYALURONATE; .ALPHA.-TOCOPHEROL ACETATE; ANGELICA ACUTILOBA ROOT; PERILLA FRUTESCENS LEAF; POLYQUATERNIUM-51 (2-METHACRYLOYLOXYETHYL PHOSPHORYLCHOLINE/N-BUTYL METHACRYLATE; 3:7); PANAX GINSENG ROOT; SAXIFRAGA STOLONIFERA LEAF; GINKGO BILOBA LEAF

cle de peau BEAUTE UV PROTECTIVE FOR BODY N

Drug Facts

Active Ingredients | Purpose
Ensulizole 2.0% | Sunscreen
Octisalate 5.0% | Sunscreen
Octocrylene 5.0% | Sunscreen
Zinc Oxide 19.4% | Sunscreen

Uses

- helps prevent sunburn
- if used as directed with other sun protection measures (see Directions), decreases the risk of skin cancer and early skin aging caused by the sun

Warnings

For external use only

Do not use on damaged or broken skin

Stop use and ask a doctor if rash occurs

Keep out of reach of children. If product is swallowed, get medical help or contact a Poison Control Center right away.

WARNINGS AND PRECAUTIONS

Flammable: Do not use near heat, flame, or while smoking

Directions

For sunscreen use:

- apply liberally 15 minutes before sun exposure
- Reapply:

• after 80 minutes of swimming or sweating

• immediately after towel drying

• at least every 2 hours

- Sun Protection Measures. Spending time in the sun increases your risk of skin cancer and early skin aging. To decrease this risk, regularly use a sunscreen with a Broad Spectrum SPF of 15 or higher and other sun protection measures including:

• limit time in the sun, especially from 10 a.m. - 2 p.m.

• wear long-sleeve shirts, pants, hats, and sunglasses

- children under 6 months: Ask a doctor

Uses

WATER･DIMETHICONE･DIISOPROPYL SEBACATE･GLYCERIN･ALCOHOL DENAT.･TRISILOXANE･PEG-9 POLYDIMETHYLSILOXYETHYL DIMETHICONE･SILICA･ISOPROPYL MYRISTATE･DIPHENYLSILOXY PHENYL TRIMETHICONE･ISODODECANE･TRIMETHYLSILOXYSILICATE･TRIETHANOLAMINE･DEXTRIN PALMITATE･TREHALOSE･MENTHA PIPERITA (PEPPERMINT) LEAF EXTRACT･RUBUS SUAVISSIMUS (RASPBERRY) LEAF EXTRACT･GLYCINE･PEG/PPG-14/7 DIMETHYL ETHER･HYDRANGEA SERRATA LEAF EXTRACT･THYMUS SERPYLLUM EXTRACT･SODIUM ACETYLATED HYALURONATE･AMINOETHANESULFINIC ACID･SODIUM HYALURONATE･TOCOPHERYL ACETATE･ANGELICA ACUTILOBA ROOT EXTRACT･HYDROLYZED CONCHIOLIN PROTEIN･HYDROLYZED SILK･PERILLA OCYMOIDES LEAF EXTRACT･POLYQUATERNIUM-51･PANAX GINSENG ROOT EXTRACT･SAXIFRAGA SARMENTOSA EXTRACT･GINKGO BILOBA LEAF EXTRACT･SCUTELLARIA BAICALENSIS ROOT EXTRACT･GARCINIA MANGOSTANA BARK EXTRACT･DISTEARDIMONIUM HECTORITE･HYDROGEN DIMETHICONE･ISOSTEARIC ACID･BUTYLENE GLYCOL･DISODIUM EDTA･SORBITAN SESQUIISOSTEARATE･ALCOHOL･TOCOPHEROL･BHT･SODIUM METABISULFITE･SYNTHETIC FLUORPHLOGOPITE･THEANINE･SYZYGIUM JAMBOS LEAF EXTRACT･PHENOXYETHANOL･FRAGRANCE･RED 33･YELLOW 5･YELLOW 6･

Other information

- protect this product in this container from excessive heat and direct sunlight

Questions or Comments?

Call toll free 1-800-906-7503

PRINCIPAL DISPALY PANEL - 100 mL Container

clé de peau

BEAUTÉ

UV PROTECTIVE EMULSION FOR BODY n

60+

BROAD SPECTRUM

SPF 60+

WATER RESISTANT

(80 MINUTES)

SUNSCREEN

100 mL 3.3 FL. OZ.